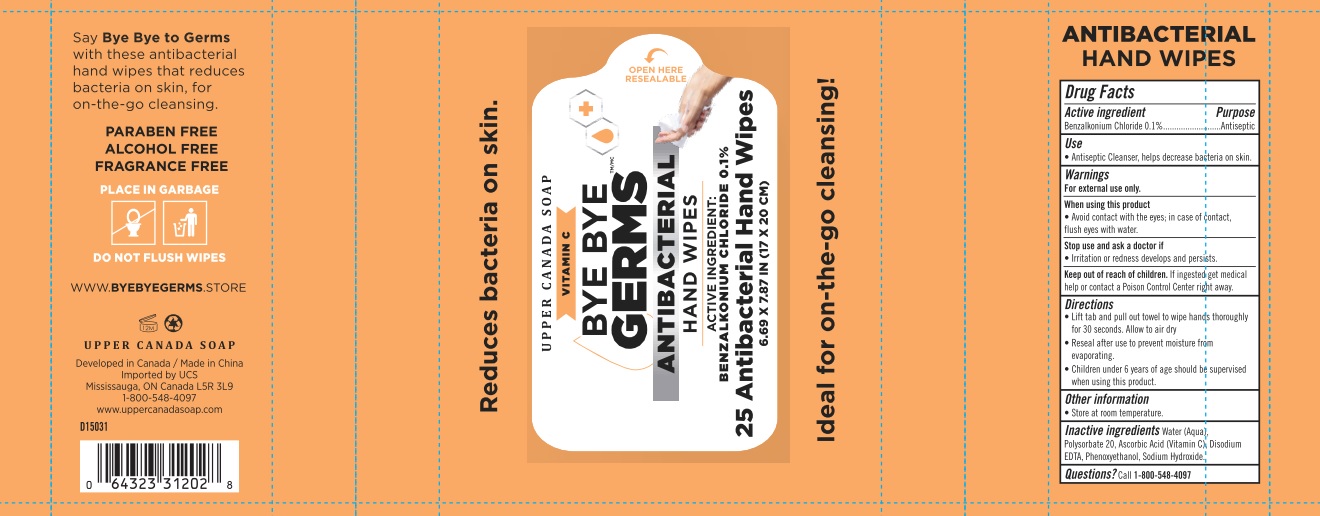 DRUG LABEL: Antibacterial Hand Wipes
NDC: 78936-022 | Form: CLOTH
Manufacturer: Hangzhou Caring Cleaning Commodity Co., LTD.
Category: otc | Type: HUMAN OTC DRUG LABEL
Date: 20201027

ACTIVE INGREDIENTS: BENZALKONIUM CHLORIDE 0.1 1/1 1
INACTIVE INGREDIENTS: WATER; POLYSORBATE 20; ASCORBIC ACID; EDETATE DISODIUM ANHYDROUS; PHENOXYETHANOL; SODIUM HYDROXIDE

Drug Facts

Active ingredient

Benzalkonium Chloride 0.1%

Purpose

Antiseptic

Use

Antiseptic Cleanser, helps decrease bacteria on skin.

Warnings

For external use only.

When using this product

Avoid contact with the eyes; in case of contact, flush eyes with water

Stop use and ask a doctor if

irritation or redness develops and persists.

Keep out of reach of children.

If ingested get medical help or contact a Poison Control Center right away.

Directions

- Lift tab and poull out towel to wipe hands thoroughly for 30 seconds. Allow to air dry.
- Reseal after use to prevent moisture from evaporating.
- Children under 6 years of age should be supervised when using this product.

Other information

- store at room temperature.

Inactive ingredients

Water (Aqua), Polysorbate 20, Ascorbic Acid (Vitamin C), Disodium EDTA, Phenoxyethanol, Sodium Hydroxide.